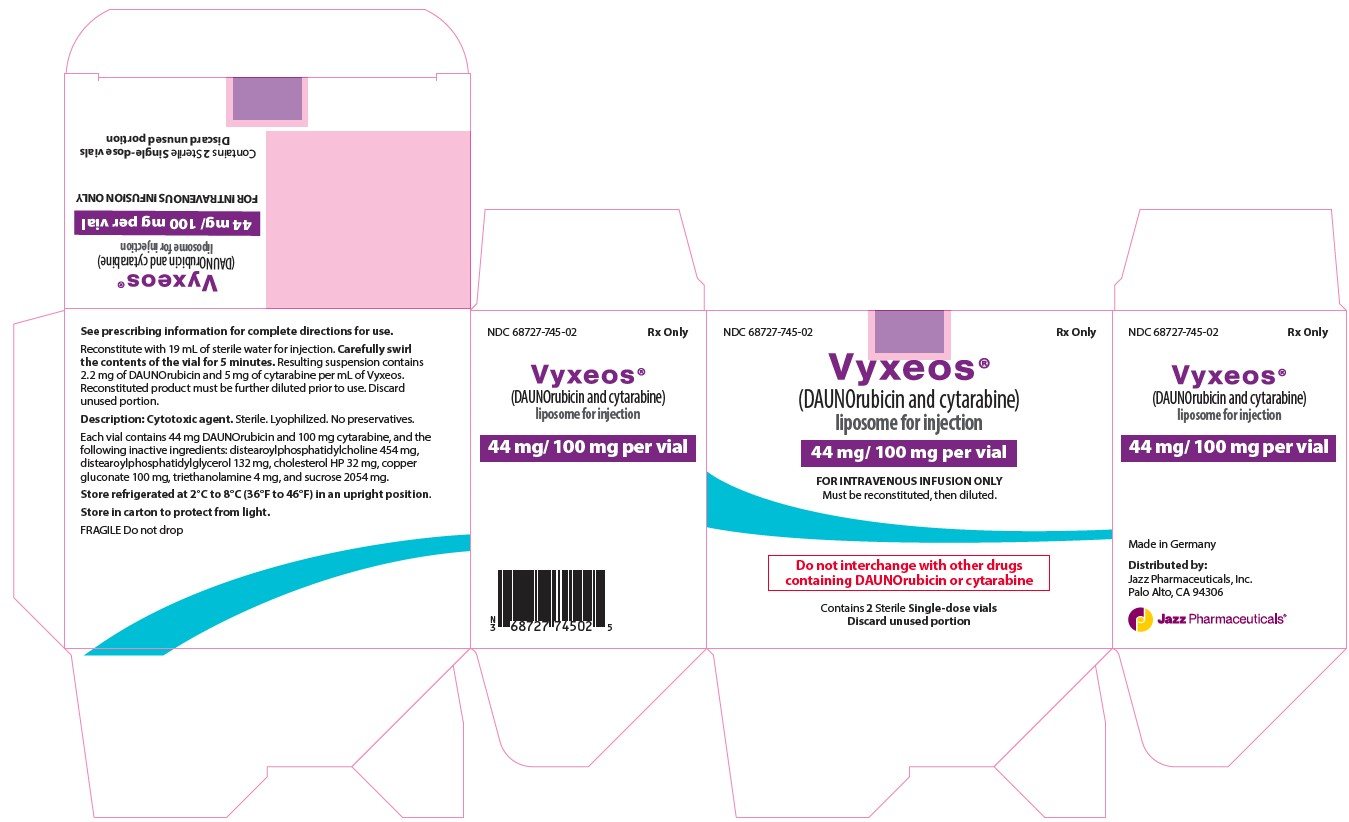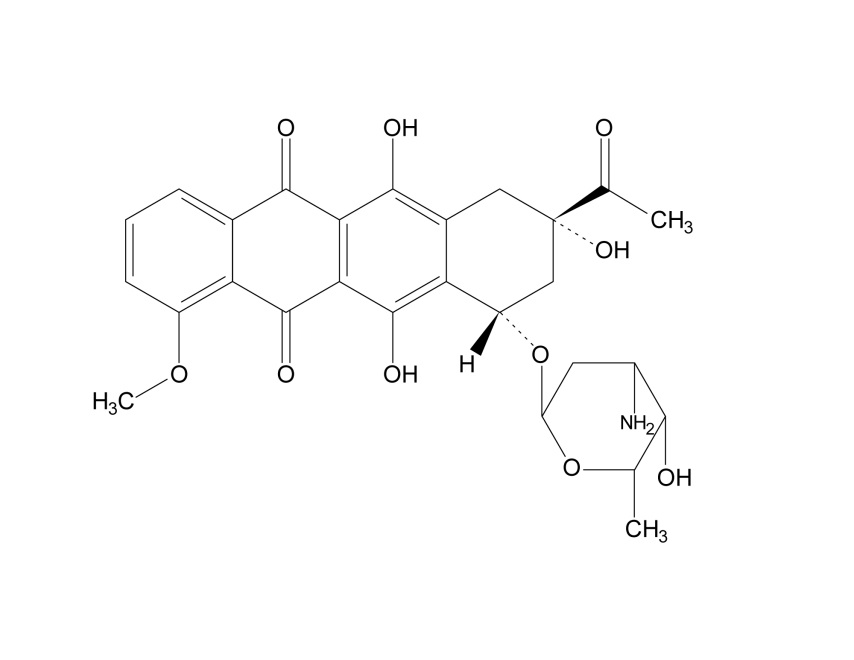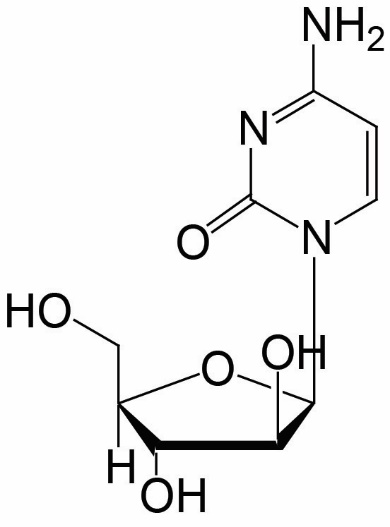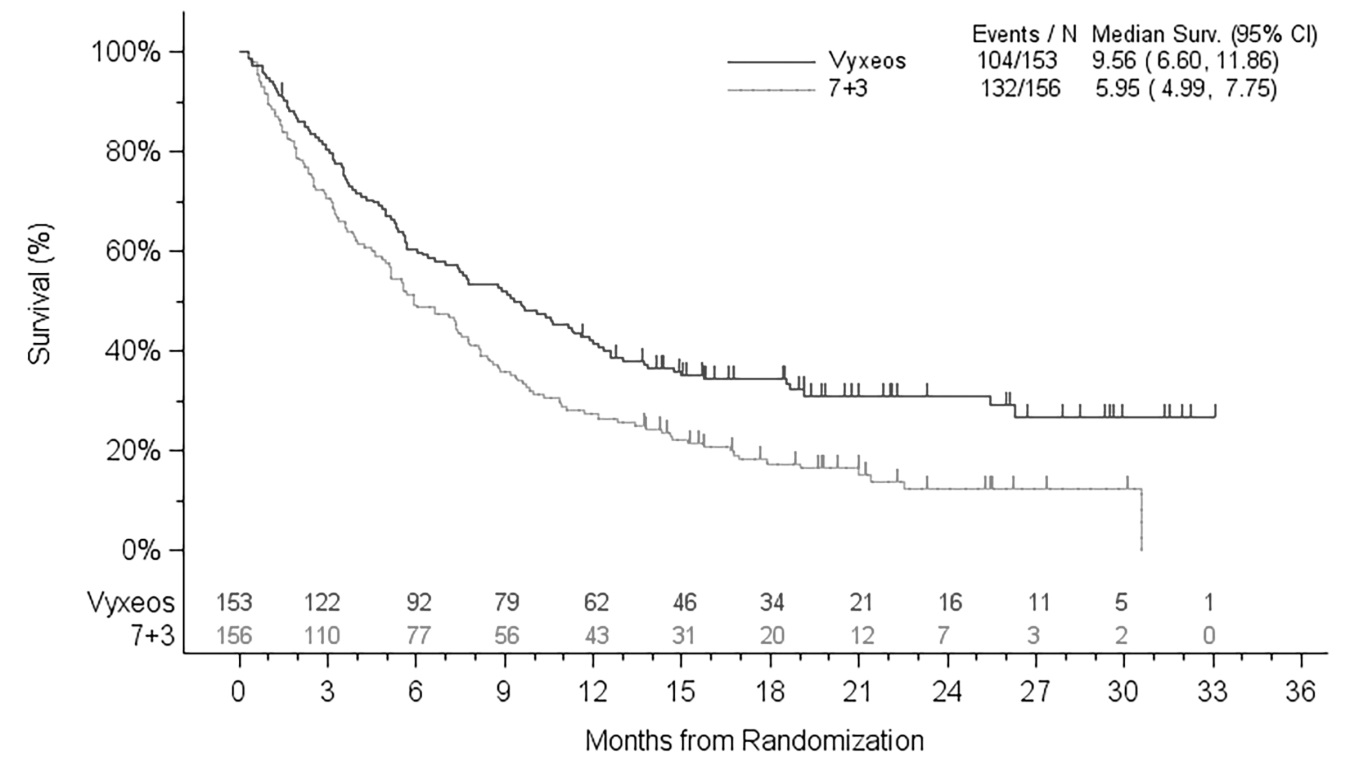 DRUG LABEL: VYXEOS
NDC: 68727-745 | Form: INJECTION, POWDER, LYOPHILIZED, FOR SUSPENSION
Manufacturer: Jazz Pharmaceuticals, Inc.
Category: prescription | Type: HUMAN PRESCRIPTION DRUG LABEL
Date: 20260130

ACTIVE INGREDIENTS: CYTARABINE 100 mg/20 mL; DAUNORUBICIN 44 mg/20 mL
INACTIVE INGREDIENTS: DISTEAROYLPHOSPHATIDYLCHOLINE, DL- 454 mg/20 mL; DISTEAROYLPHOSPHATIDYLGLYCEROL, DL- 132 mg/20 mL; CHOLESTEROL 32 mg/20 mL; COPPER GLUCONATE 100 mg/20 mL; TROLAMINE 4 mg/20 mL; SUCROSE 2054 mg/20 mL

HIGHLIGHTS OF PRESCRIBING INFORMATION

These highlights do not include all the information needed to use VYXEOS safely and effectively. See full prescribing information for VYXEOS.
VYXEOS® (daunorubicin and cytarabine) liposome for injection, for intravenous use
Initial U.S. Approval: 2017

WARNING: DO NOT INTERCHANGE WITH OTHER DAUNORUBICIN AND/OR CYTARABINE-CONTAINING PRODUCTS

See full prescribing information for complete boxed warning.

- VYXEOS has different dosage recommendations than daunorubicin hydrochloride injection, cytarabine injection, daunorubicin citrate liposome injection, and cytarabine liposome injection. Verify drug name and dose prior to preparation and administration to avoid dosing errors (5.1).

1 INDICATIONS AND USAGE

VYXEOS is a liposomal combination of daunorubicin, an anthracycline topoisomerase inhibitor, and cytarabine, a nucleoside metabolic inhibitor, that is indicated for the treatment of newly diagnosed therapy-related acute myeloid leukemia (t-AML) or AML with myelodysplasia-related changes (AML-MRC) in adults and pediatric patients 1 year and older. (1)

2 DOSAGE AND ADMINISTRATION

- Induction: VYXEOS (daunorubicin 44 mg/m^2 and cytarabine 100 mg/m^2) liposome via intravenous infusion over 90 minutes on days 1, 3, and 5 and on days 1 and 3 for subsequent cycles of induction, if needed. (2.1)
- Consolidation: VYXEOS (daunorubicin 29 mg/m^2 and cytarabine 65 mg/m^2) liposome via intravenous infusion over 90 minutes on days 1 and 3. (2.1)
- See Full Prescribing Information for instructions on preparation and administration. (2.3, 2.4)

3 DOSAGE FORMS AND STRENGTHS

For injection: 44 mg daunorubicin and 100 mg cytarabine encapsulated in liposomes as a lyophilized cake in a single-dose vial for reconstitution. (3)

4 CONTRAINDICATIONS

- History of serious hypersensitivity to daunorubicin, cytarabine or any component of the formulation. (4)

5 WARNINGS AND PRECAUTIONS

- Hemorrhage: Serious or fatal hemorrhagic events with associated prolonged thrombocytopenia have occurred with VYXEOS. Monitor blood counts regularly until recovery. (5.2)
- Cardiotoxicity: VYXEOS treatment is not recommended in patients with cardiac function that is less than normal. Discontinue VYXEOS in patients with impaired cardiac function unless the benefit of continuing treatment outweighs the risk. (2.2, 5.3)
- Hypersensitivity: If severe or life-threatening hypersensitivity reaction occurs, discontinue VYXEOS, treat according to standard of care, and monitor until signs and symptoms resolve. (2.2, 5.4)
- Tissue Necrosis: Daunorubicin has been associated with local tissue necrosis at the site of drug extravasation. Confirm intravenous access before administration. (5.6)
- Embryo-Fetal Toxicity: Can cause fetal harm. Advise females of reproductive potential of the potential risk to a fetus and to use effective contraception. (5.7, 8.1, 8.3)

6 ADVERSE REACTIONS

The most common adverse reactions (incidence ≥ 25%) are hemorrhagic events, febrile neutropenia, rash, edema, nausea, mucositis, diarrhea, constipation, musculoskeletal pain, fatigue, abdominal pain, dyspnea, headache, cough, decreased appetite, arrhythmia, pneumonia, bacteremia, chills, sleep disorders, and vomiting. (6.1)

To report SUSPECTED ADVERSE REACTIONS, contact Jazz Pharmaceuticals, Inc. at 1-800-520-5568 or FDA at 1-800-FDA-1088 or www.fda.gov/medwatch.

7 DRUG INTERACTIONS

- Monitor cardiac function more frequently when coadministered with cardiotoxic agents. (7.1)
- Monitor hepatic function more frequently when coadministered with hepatotoxic agents. (7.2)

8 USE IN SPECIFIC POPULATIONS

Lactation: Advise not to breastfeed. (8.2)

FULL PRESCRIBING INFORMATION

WARNING: DO NOT INTERCHANGE WITH OTHER DAUNORUBICIN AND/OR CYTARABINE-CONTAINING PRODUCTS

- VYXEOS has different dosage recommendations than daunorubicin hydrochloride injection, cytarabine injection, daunorubicin citrate liposome injection, and cytarabine liposome injection. Verify drug name and dose prior to preparation and administration to avoid dosing errors [see Warnings and Precautions (5.1)].

1 INDICATIONS AND USAGE

VYXEOS is indicated for the treatment of newly diagnosed therapy-related acute myeloid leukemia (t-AML) or AML with myelodysplasia-related changes (AML-MRC) in adults and pediatric patients 1 year and older.

2 DOSAGE AND ADMINISTRATION

2.1 Recommended Dosage

A full VYXEOS course consists of 1-2 cycles of Induction and up to 2 cycles of Consolidation at the dose and schedule listed in Table 1. Prior to initiating each cycle of VYXEOS, calculate the prior cumulative anthracycline exposure for the patient [see Warnings and Precautions (5.3)]. Administer prophylactic anti-emetics before treatment with VYXEOS.

Table 1: Dose and Schedule for VYXEOS
Cycle | VYXEOS Dose and Schedule
First Induction | (daunorubicin 44 mg/m^2 and cytarabine 100 mg/m^2) liposome days 1, 3, and 5
Second Inductiona | (daunorubicin 44 mg/m^2 and cytarabine 100 mg/m^2) liposome days 1 and 3
Consolidation | (daunorubicin 29 mg/m^2 and cytarabine 65 mg/m^2) liposome days 1 and 3

a Only for patients failing to achieve a response with the first induction cycle.

For the first cycle of induction, the recommended dose of VYXEOS is (daunorubicin 44 mg/m^2 and cytarabine 100 mg/m^2) liposome administered via intravenous infusion over 90 minutes on days 1, 3, and 5. Prior to initiating induction, assess cardiac function and obtain liver and renal function studies. For patients who do not achieve remission with the first induction cycle, a second induction cycle may be administered 2 to 5 weeks after the first if there was no unacceptable toxicity with VYXEOS. The recommended dose for the second induction cycle of VYXEOS is (daunorubicin 44 mg/m^2 and cytarabine 100 mg/m^2) liposome administered via intravenous infusion over 90 minutes on days 1 and 3.

Administer the first consolidation cycle 5 to 8 weeks after the start of the last induction. The recommended dose for each cycle of consolidation therapy is VYXEOS (daunorubicin 29 mg/m^2 and cytarabine 65 mg/m^2) liposome administered via intravenous infusion over 90 minutes on days 1 and 3.

Assess cardiac function, complete blood counts, liver and renal function before each consolidation cycle. Do not start VYXEOS consolidation until the absolute neutrophil count recovers to greater than 0.5 Gi/L and the platelet count recovers to greater than 50 Gi/L in the absence of unacceptable toxicity. Administer the second consolidation cycle 5 to 8 weeks after the start of the first consolidation cycle in patients who do not show disease progression or unacceptable toxicity to VYXEOS.

2.2 Dosage Modification

Missed Doses of VYXEOS

If a planned dose of VYXEOS is missed, administer the dose as soon as possible and adjust the dosing schedule accordingly, maintaining the treatment interval.

Hypersensitivity Reactions

For hypersensitivity reactions of any grade/severity, interrupt VYXEOS infusion immediately and manage symptoms. Reduce the rate of infusion or discontinue treatment as outlined below [see Warnings and Precautions (5.4)].

- Mild symptoms: Once symptoms resolve, reinitiate infusion at half the prior rate of infusion. Consider premedication with antihistamines and/or corticosteroids for subsequent doses of VYXEOS.
- Moderate symptoms: Do not reinitiate infusion. For subsequent doses of VYXEOS, premedicate with antihistamines and/or corticosteroids prior to initiating infusion at same rate.
- Severe/life-threatening symptoms: Permanently discontinue VYXEOS treatment, treat according to the standard of care to manage symptoms, and monitor patient until symptoms resolve.

Cardiotoxicity

Discontinue VYXEOS in patients who exhibit impaired cardiac function unless the benefit of continuing treatment outweighs the risk [see Warnings and Precautions (5.3)].

2.3 Preparation and Handling Instructions

VYXEOS is a hazardous drug. Follow applicable special handling and disposal procedures. 1 VYXEOS is supplied as a single-dose vial and does not contain any preservatives. Do not save any unused portions for later administration.

Reconstitute and further dilute VYXEOS prior to intravenous infusion.

Reconstitution:

- Calculate the VYXEOS dose based on daunorubicin and individual patient's body surface area (BSA).
- Calculate the number of vials of VYXEOS based on the daunorubicin dose.
- Remove the appropriate number of vials of VYXEOS from the refrigerator and equilibrate to the room temperature for 30 minutes.
- Then, reconstitute each vial with 19 mL of Sterile Water for Injection using a sterile syringe and immediately thereafter start a 5-minute timer.
- Carefully swirl the contents of the vial for 5 minutes while gently inverting the vial every 30 seconds.
- Do not heat, vortex, or shake vigorously.
- After reconstitution, let rest for 15 minutes.
- The reconstituted product should be an opaque, purple, homogeneous dispersion, essentially free from visible particulates. After reconstitution (but before final dilution), each mL will contain 2.2 mg of daunorubicin and 5 mg of cytarabine.
- Use the reconstituted solution immediately. If needed, store the reconstituted solution in the vial refrigerated at 2ºC to 8ºC (36°F to 46°F) for up to 4 hours. Note that the reconstituted product in the vial and the reconstituted product which has been diluted into an infusion solution are stable for a total of 4 hours (not 4 hours each) when stored at 2°C to 8°C.

Dilution:

- Calculate the volume of reconstituted VYXEOS required using the following formula:
  [volume required (mL) = dose of daunorubicin (mg/m^2) X patient's BSA (m^2) ÷ 2.2 (mg/mL)]
- Gently invert each vial 5 times prior to withdrawing the reconstituted product for further dilution.
- Aseptically withdraw the calculated volume of the reconstituted product from the vial(s) with a sterile syringe and transfer it to an infusion bag containing 500 mL of 0.9% Sodium Chloride Injection, USP or 5% Dextrose Injection, USP. There may be residual product remaining in the vial. Discard unused portion.
- Gently invert the bag to mix the solution. The dilution of the reconstituted product results in a deep purple, translucent, homogeneous dispersion, free from visible particulates.
- If the diluted infusion solution is not used immediately, store in a refrigerator at 2ºC to 8ºC (36°F to 46°F) for up to 4 hours. If the reconstituted solution in the vial was stored for 4 hours, the diluted infusion solution must be used immediately and cannot be stored for an additional 4 hours.
- Parenteral drug products should be inspected visually for particulate matter and discoloration prior to administration, whenever solution and container permit. Only solutions without visible particles should be used.

2.4 Administration Instructions

- For intravenous use only.
- Do not mix VYXEOS with or administer as an infusion with other drugs.
- Administer VYXEOS by constant intravenous infusion over 90 minutes via an infusion pump through a central venous catheter or a peripherally inserted central catheter. An in-line membrane filter may be used for the intravenous infusion of Vyxeos, provided the minimum pore diameter of the filter is greater than or equal to 15 microns.
- Flush the line after administration with 0.9% Sodium Chloride Injection, USP or 5% Dextrose Injection, USP.

3 DOSAGE FORMS AND STRENGTHS

VYXEOS is a sterile, preservative-free, purple, lyophilized cake for reconstitution supplied in a single-dose clear glass vial as follows:

- For injection: 44 mg daunorubicin and 100 mg cytarabine encapsulated in liposomes.

4 CONTRAINDICATIONS

The use of VYXEOS is contraindicated in patients with the following:

- History of serious hypersensitivity reaction to cytarabine, daunorubicin, or any component of the formulation [see Warnings and Precautions (5.4)].

5 WARNINGS AND PRECAUTIONS

5.1 Do Not Interchange With Other Daunorubicin And/Or Cytarabine-Containing Products

Due to substantial differences in the pharmacokinetic parameters, the dose and schedule recommendations for VYXEOS are different from those for daunorubicin hydrochloride injection, cytarabine injection, daunorubicin citrate liposome injection, and cytarabine liposome injection. Verify drug name and dose prior to preparation and administration to avoid dosing errors. Do not substitute other preparations of daunorubicin or cytarabine for VYXEOS.

5.2 Hemorrhage

Serious or fatal hemorrhage events, including fatal central nervous system (CNS) hemorrhages, associated with prolonged severe thrombocytopenia, have occurred in patients treated with VYXEOS. In Study 1 (NCT01696084), the incidence of any grade hemorrhagic events during the entire treatment period was 74% of patients on the VYXEOS arm and 56% on the control arm. The most frequently reported hemorrhagic event was epistaxis (36% in VYXEOS arm and 18% in control arm). Grade 3 or greater events occurred in 12% of VYXEOS treated patients and 8% of patients treated with 7+3. Fatal treatment-emergent CNS hemorrhage not in the setting of progressive disease occurred in 2% of patients on the VYXEOS arm and in 0.7% of patients on the control arm. Monitor blood counts regularly until recovery and administer platelet transfusion support as required [see Adverse Reactions (6.1)].

5.3 Cardiotoxicity

VYXEOS contains the anthracycline daunorubicin, which has a known risk of cardiotoxicity. Prior therapy with anthracyclines, pre-existing cardiac disease, previous radiotherapy to the mediastinum, or concomitant use of cardiotoxic drugs may increase the risk of daunorubicin-induced cardiac toxicity. Prior to administering VYXEOS, obtain an electrocardiogram (ECG) and assess cardiac function by multi-gated radionuclide angiography (MUGA) scan or echocardiography (ECHO). Repeat MUGA or ECHO determinations of left ventricular ejection fraction (LVEF) prior to consolidation with VYXEOS and as clinically required. Discontinue VYXEOS in patients with impaired cardiac function unless the benefit of initiating or continuing treatment outweighs the risk. VYXEOS treatment is not recommended in patients with LVEF that is less than normal.

Total cumulative doses of non-liposomal daunorubicin greater than 550 mg/m^2 have been associated with an increased incidence of drug-induced congestive heart failure. The tolerable limit appears lower (400 mg/m^2) in patients who received radiation therapy to the mediastinum.

Calculate the lifetime cumulative anthracycline exposure prior to each cycle of VYXEOS. VYXEOS treatment is not recommended in patients whose lifetime anthracycline exposure has reached the maximum cumulative limit. The exposure to daunorubicin following each cycle of VYXEOS is shown in Table 2.

Table 2: Cumulative Exposure of Daunorubicin per Cycle of VYXEOS
Therapy | Daunorubicin per Dose | Number of Doses per Cycle | Daunorubicin per Cycle
First Induction Cycle | 44 mg/m^2 | 3 | 132 mg/m^2
Second Induction Cycle | 44 mg/m^2 | 2 | 88 mg/m^2
Each Consolidation Cycle | 29 mg/m^2 | 2 | 58 mg/m^2

5.4 Hypersensitivity Reactions

Serious or fatal hypersensitivity reactions, including anaphylactic reactions, have been reported with daunorubicin and cytarabine. Monitor patients for hypersensitivity reactions. If a mild or moderate hypersensitivity reaction occurs, interrupt or slow the rate of infusion with VYXEOS and manage symptoms. If a severe or life-threatening hypersensitivity reaction occurs, discontinue VYXEOS permanently, treat symptoms according to the standard of care, and monitor until symptoms resolve [see Dosage and Administration (2.2)].

5.5 Copper Overload

Reconstituted VYXEOS contains 5 mg/mL copper gluconate, of which 14% is elemental copper. There is no clinical experience with VYXEOS in patients with Wilson’s disease or other copper-related metabolic disorders. The maximum theoretical total exposure of copper under the recommended VYXEOS dosing regimen is 106 mg/m^2 [see Dosage and Administration (2.1)]. Consult with a hepatologist and nephrologist with expertise in managing acute copper toxicity in patients with Wilson’s disease treated with VYXEOS. Monitor total serum copper, serum non-ceruloplasmin bound copper, 24-hour urine copper levels and serial neuropsychological examinations in these patients. Use VYXEOS in patients with Wilson’s disease only if the benefits outweigh the risks. Discontinue VYXEOS in patients with signs or symptoms of acute copper toxicity.

5.6 Tissue Necrosis

Daunorubicin has been associated with severe local tissue necrosis at the site of drug extravasation. Administer VYXEOS by the intravenous route only. Confirm patency of the intravenous access before administration. Do not administer by the intramuscular or subcutaneous route.

5.7 Embryo-Fetal Toxicity

Based on its mechanism of action and findings from animal studies with daunorubicin and cytarabine, VYXEOS can cause embryo-fetal harm when administered to a pregnant woman. There are no adequate and well-controlled studies of VYXEOS, daunorubicin, or cytarabine in pregnant women. Daunorubicin and cytarabine are reproductive and developmental toxicants in multiple species (mice, rats, and/or dogs), starting at a dose that was approximately 0.02 times the exposure in patients at the recommended human dose on a mg/m^2 basis. Patients should be advised to avoid becoming pregnant while taking VYXEOS. If this drug is used during pregnancy or if the patient becomes pregnant while taking this drug, apprise the patient of the potential risk to a fetus. Advise females and males of reproductive potential to use effective contraception during treatment and for 6 months following the last dose of VYXEOS [see Use in Specific Populations (8.1) and (8.3)].

6 ADVERSE REACTIONS

The following adverse reactions are discussed in greater detail in other sections of the labeling:

- Hemorrhage [see Warnings and Precautions (5.2)]
- Cardiotoxicity [see Warnings and Precautions (5.3)]
- Hypersensitivity Reactions [see Warnings and Precautions (5.4)]
- Copper Overload [see Warnings and Precautions (5.5)]
- Tissue Necrosis [see Warnings and Precautions (5.6)]

6.1 Clinical Trials Experience

Because clinical trials are conducted under widely varying conditions, adverse reaction rates observed in the clinical trials of a drug cannot be directly compared to rates in the clinical trials of another drug and may not reflect the rates observed in practice.

The safety of VYXEOS was determined in a randomized trial for adults with newly diagnosed t‑AML or AML-MRC [see Clinical Studies (14)] which included 153 patients treated with VYXEOS and 151 patients treated with a standard combination of cytarabine and daunorubicin (7+3). At study entry, patients were required to have a LVEF of at least 50% and a prior lifetime cumulative anthracycline exposure less than 368 mg/m^2 daunorubicin (or equivalent). On study, the median number of cycles administered was 2 (range, 1–4 cycles) on the VYXEOS arm and 1 (range, 1–4 cycles) on the control arm. The median cumulative daunorubicin dose was 189 mg/m^2 (range, 44–337 mg/m^2) on the VYXEOS arm and 186 mg/m^2 (range, 44–532 mg/m^2) on the control arm.

Nine patients each on the VYXEOS arm (6%) and the control arm (6%) had a fatal adverse reaction on treatment or within 30 days of therapy that was not in the setting of progressive disease. Fatal adverse reactions on the VYXEOS arm included infection, CNS hemorrhage, and respiratory failure. Overall, all-cause day-30 mortality was 6% in the VYXEOS arm and 11% in the control arm. During the first 60 days of the study, 14% (21/153) of patients died in the VYXEOS arm vs. 21% (32/151) of patients in the 7+3 treatment group.

The most common serious adverse reactions (incidence ≥ 5%) on the VYXEOS arm were dyspnea, myocardial toxicity, sepsis, pneumonia, febrile neutropenia, bacteremia and hemorrhage. Adverse reactions led to discontinuation of VYXEOS in 18% (28/153) of patients, and 13% (20/151) in the control arm. The adverse reactions leading to discontinuation on the VYXEOS arm included prolonged cytopenias, infection, cardiotoxicity, respiratory failure, hemorrhage (GI and CNS), renal insufficiency, colitis, and generalized medical deterioration. The most common adverse reactions (incidence ≥ 25%) in patients on the VYXEOS arm were hemorrhagic events, febrile neutropenia, rash, edema, nausea, mucositis, diarrhea, constipation, musculoskeletal pain, fatigue, abdominal pain, dyspnea, headache, cough, decreased appetite, arrhythmia, pneumonia, bacteremia, chills, sleep disorders, and vomiting. The incidences of common adverse drug reactions during the induction phase in Study 1 are presented in Table 3.

Table 3: Common Adverse Reactions (≥ 10% Incidence in the VYXEOS arm) During the Induction Phase
Adverse Reaction a | All Grades b |  | Grades 3 to 5 b
 | VYXEOS; N=153; n (%) | 7+3; N=151; n (%) | VYXEOS; N=153; n (%) | 7+3; N=151; n (%)
Hemorrhage a | 107 (70) | 74 (49) | 15 (10) | 9 (6)
Febrile Neutropenia | 104 (68) | 103 (68) | 101 (66) | 102 (68)
Rash a | 82 (54) | 55 (36) | 8 (5) | 2 (1)
Edema a | 78 (51) | 90 (60) | 2 (2) | 5 (3)
Nausea | 72 (47) | 79 (52) | 1 (1) | 1 (1)
Diarrhea/Colitis a | 69 (45) | 100 (66) | 4 (3) | 10 (7)
Mucositis a | 67 (44) | 69 (46) | 2 (1) | 7 (5)
Constipation | 61 (40) | 57 (38) | 0 | 0
Musculoskeletal pain a | 58 (38) | 52 (34) | 5 (3) | 4 (3)
Abdominal pain a | 51 (33) | 45 (30) | 3 (2) | 3 (2)
Cough a | 51 (33) | 34 (23) | 0 | 1 (1)
Headache a | 51 (33) | 36 (24) | 2 (1) | 1 (1)
Dyspnea a | 49 (32) | 51 (34) | 17 (11) | 15 (10)
Fatigue a | 49 (32) | 58 (38) | 8 (5) | 8 (5)
Arrhythmia a | 46 (30) | 41 (27) | 10 (7) | 7 (5)
Decreased appetite | 44 (29) | 57 (38) | 2 (1) | 5 (3)
Pneumonia (excluding fungal) a | 39 (26) | 35 (23) | 30 (20) | 26 (17)
Sleep disorders a | 38 (25) | 42 (28) | 2 (1) | 1 (1)
Bacteremia (excluding sepsis) a | 37 (24) | 37 (25) | 35 (23) | 31 (21)
Vomiting a | 37 (24) | 33 (22) | 0 | 0
Chills | 35 (23) | 38 (25) | 0 | 0
Hypotension a | 30 (20) | 32 (21) | 7 (5) | 1 (1)
Non-conduction cardiotoxicity a | 31 (20) | 27 (18) | 13 (9) | 15 (10)
Dizziness a | 27 (18) | 26 (17) | 1 (1) | 0
Fungal infection a | 27 (18) | 19 (13) | 11 (7) | 9 (6)
Hypertension a | 28 (18) | 22 (15) | 15 (10) | 8 (5)
Hypoxia a | 28 (18) | 31 (21) | 19 (12) | 23 (15)
Upper respiratory infections (excluding fungal) a | 28 (18) | 19 (13) | 4 (3) | 1 (1)
Chest pain a | 26 (17) | 22 (15) | 5 (3) | 0
Pyrexia | 26 (17) | 23 (15) | 1 (1) | 2 (1)
Catheter/device/injection site reaction a | 24 (16) | 15 (10) | 0 | 0
Delirium a | 24 (16) | 33 (22) | 4 (3) | 9 (6)
Pleural effusion | 24 (16) | 25 (17) | 3 (2) | 2 (1)
Anxiety | 21 (14) | 16 (11) | 0 | 0
Pruritus a | 23 (15) | 14 (9) | 0 | 0
Sepsis (excluding fungal) a | 17 (11) | 20 (13) | n/a
Hemorrhoids | 16 (11) | 12 (8) | 0 | 0
Petechiae | 17 (11) | 17 (11) | 0 | 0
Renal insufficiency a | 17 (11) | 17 (11) | 7 (5) | 7 (5)
Transfusion reactions a | 17 (11) | 16 (11) | 3 (2) | 1 (1)
Visual impairment (except bleeding) a | 16 (11) | 8 (5) | 0 | 0

a Grouped terms: Hemorrhage: Anal hemorrhage, Blood blister, Blood urine present, Breast hematoma, Catheter site bruise, Catheter site hemorrhage, Central nervous system hemorrhage, Cerebral hematoma, Cerebral hemorrhage, Coagulopathy, Conjunctival hemorrhage, Contusion, Ecchymosis, Enterocolitis hemorrhagic, Epistaxis, Gastric hemorrhage, Gastrointestinal hemorrhage, Gingival bleeding, Hematemesis, Hematochezia, Hematoma, Hematuria, Hemoptysis, Hemorrhage, Hemorrhage intracranial, Hemorrhage subcutaneous, Hemorrhage urinary tract, Hemorrhoidal hemorrhage, Lip hematoma, Lip hemorrhage, Lower gastrointestinal hemorrhage, Melena, Mouth hemorrhage, Mucosal hemorrhage, Periorbital hematoma, Periorbital hemorrhage, Pharyngeal hematoma, Pharyngeal hemorrhage, Post procedural contusion, Post procedural hematoma, Post procedural hemorrhage, Pulmonary alveolar hemorrhage, Pulmonary hemorrhage, Purpura, Rectal hemorrhage, Retinal hemorrhage, Scleral hemorrhage, Scrotal hematoma, Skin ulcer hemorrhage, Small intestinal hemorrhage, Stomatitis hemorrhagic, Subdural hematoma, Subdural hemorrhage, Subgaleal hematoma, Tongue hemorrhage, Traumatic hematoma, Upper gastrointestinal hemorrhage, Urethral hemorrhage, Vaginal hemorrhage, Vessel puncture site hemorrhage, Vitreous hemorrhage; Rash: Dermatitis, Dermatitis acneiform, Dermatitis allergic, Dermatitis contact, Eczema, Erythema nodosum, Exfoliative rash, Psoriasis, Rash, Rash erythematous, Rash follicular, Rash generalized, Rash macular, Rash maculo-papular, Rash papular, Rash pruritic, Rash pustular, Skin exfoliation; Edema: Face edema, Fluid overload, Fluid retention, Generalized edema, Localized edema, Edema, Edema peripheral, Penile edema, Scrotal edema, Swelling, Swelling face; Diarrhea/Colitis: Cecitis, Colitis, Diarrhea, Enterocolitis, Ileitis, Neutropenic colitis, Enteritis, Enterocolitis; Mucositis: Anal erosion, Anorectal discomfort, Duodenitis, Gastric ulcer, Gastrointestinal inflammation, Gingival pain, Gingival swelling, Gingivitis, Glossodynia, Laryngeal inflammation, Lip ulceration, Mouth ulceration, Mucosal inflammation, Mucosal ulceration, Odynophagia, Edema mouth, Esophageal ulcer, Esophagitis, Oral mucosa erosion, Oral mucosal blistering, Oral mucosal erythema, Pharyngeal ulceration, Proctalgia, Proctitis, Rectal ulcer, Stomatitis, Tongue ulceration, Oropharyngeal pain, Oral pain, Oropharyngeal discomfort, Pharyngeal erythema; Musculoskeletal pain: Arthralgia, Back pain, Bone pain, Coccydynia, Limb discomfort, Musculoskeletal chest pain, Musculoskeletal pain, Myalgia, Neck pain, Pain in extremity, Pain in jaw; Abdominal pain: Abdominal pain, Abdominal distension, Abdominal pain upper, Abdominal discomfort, Abdominal pain lower, Abdominal tenderness; Cough: Cough, Productive Cough; Headache: Headache, Sinus Headache; Dyspnea: Acute respiratory distress syndrome, Acute respiratory failure, Bronchospasm, Dyspnea, Dyspnea exertional, Respiratory distress, Respiratory failure, Wheezing; Fatigue: Fatigue, Asthenia; Arrhythmia: Arrhythmia, Arrhythmia supraventricular, Atrial fibrillation, Atrial flutter, Atrial tachycardia, Atrioventricular block first degree, Atrioventricular block second degree, Bradycardia, Bundle branch block right, Extrasystoles, Heart rate increased, Nodal arrhythmia, Nodal rhythm, Sinus arrest, Sinus arrhythmia, Sinus bradycardia, Sinus tachycardia, Supraventricular tachycardia, Tachycardia, Ventricular extrasystoles, Ventricular tachycardia; Pneumonia (excluding fungal): Lung consolidation, Lung infection, Lung infiltration, Pneumonia, Pneumonia aspiration, Pneumonia bacterial, Pneumonia klebsiella, Pneumonia pseudomonas aeruginosa, Pneumonia viral; Sleep disorders: Abnormal dreams, Insomnia, Nightmare, Sleep apnea syndrome, Sleep disorder; Bacteremia (excluding sepsis): Bacillus test positive, Bacteremia, Bacteroides bacteremia, Corynebacterium test positive, Enterobacter bacteremia, Enterococcal bacteremia, Enterococcus test positive, Escherichia bacteremia, Klebsiella bacteremia, Pseudomonal bacteremia, Pseudomonas test positive, Staphylococcal bacteremia, Staphylococcus test positive, Stomatococcus test positive, Streptococcal bacteremia, Streptococcus test positive, Escherichia test positive, Klebsiella test positive; Vomiting: Retching, Vomiting; Hypotension: Hypotension, Orthostatic hypotension; Non-conduction cardiotoxicity: Acute coronary syndrome, Acute endocarditis, Acute myocardial infarction, Angina pectoris, Aortic valve incompetence, Cardiac arrest, Cardiac failure, Cardiac failure congestive, Cardiac murmur, Cardiogenic shock, Cardiomegaly, Cardiomyopathy, Cardiotoxicity, Cytotoxic cardiomyopathy, Diastolic dysfunction, Dilatation atrial, Dilatation ventricular, Ejection fraction decreased, Endocarditis, Left ventricular dysfunction, Mitral valve incompetence, Myocardial infarction, Pericardial effusion, Pericarditis, Restrictive cardiomyopathy, Right ventricular hypertrophy; Dizziness: Dizziness, Dizziness postural, Dizziness exertional; Fungal infection: Aspergillosis, Bronchopulmonary aspergillosis, Candida test positive, Candidiasis, Fungemia, Fungal infection, Fungal skin infection, Intertrigo candida, Lower respiratory tract infection fungal, Oral candidiasis, Pneumonia fungal, Pulmonary mycosis, Sinusitis fungal, Skin candida, Tinea cruris, Tinea infection, Vulvovaginal mycotic infection, Wound infection fungal, Zygomycosis, Mycotic aneurysm; Hypertension: Blood pressure increased, Hypertension; Hypoxia: Hypoxia, Oxygen saturation decreased; Upper respiratory infection (excluding fungal): Acute sinusitis, Chronic sinusitis, Increased upper airway secretion, Nasal congestion, Pharyngitis, Rhinitis, Rhinorrhea, Sinus congestion, Sinusitis, Sinusitis bacterial, Upper respiratory tract congestion, Upper respiratory tract infection, Upper-airway cough syndrome, Viral upper respiratory tract infection; Chest pain: Chest discomfort, Chest pain, Non-cardiac chest pain, Pleuritic pain; Catheter/device/injection site reaction: Catheter site discharge, Catheter site erosion, Catheter site erythema, Catheter site inflammation, Catheter site edema, Catheter site pain, Catheter site pruritus, Catheter site rash, Infusion site edema, Infusion site pain, Infusion site vesicles, Catheter site related reaction; Delirium: Cognitive disorder, Confusional state, Delirium; Pruritis: Anal pruritis, Ear pruritis, Pruritis, Pruritis generalized; Sepsis (excluding fungal): Enterobacter sepsis, Escherichia sepsis, Klebsiella sepsis, Neutropenic sepsis, Sepsis, Septic shock, Staphylococcal sepsis, Streptococcal sepsis, Urosepsis, Viral sepsis; Renal insufficiency: Acute prerenal failure, Azotemia, Oliguria, Renal failure, Renal failure acute, Renal failure chronic; Transfusion reactions: Allergic transfusion reaction, Febrile non-hemolytic transfusion reaction, Transfusion reaction; Visual impairment (except bleeding): Photophobia, Photopsia, Photosensitivity reaction, Retinal tear, Scintillating scotoma, Uveitis, Vision blurred, Visual acuity reduced, Visual impairment, Vitreous detachment, Vitreous floaters

b Adverse reactions were graded using NCI CTCAE version 3.0.

During the consolidation phase (both consolidation cycles pooled) the two most common adverse reactions on the VYXEOS arm are the same as those during induction, hemorrhagic events and febrile neutropenia. These occurred at lower rates in the pooled consolidation phase (43% and 29%, respectively), compared to the induction phase. All of the common adverse reactions (≥ 10% incidence in the VYXEOS arm) seen in the pooled consolidation phase were also seen in the induction phase. These occurred at lower incidence in the consolidation phase, with the exception of chills, dizziness and pyrexia, where the incidences were relatively similar across the induction and consolidation cycles.

Other notable adverse drug reactions that occurred in less than 10% of patients treated with VYXEOS during induction or consolidation included:

- Ear and labyrinth disorders: Deafness, Deafness unilateral
- Eye Disorders: Eye conjunctivitis, Dry eye, Eye edema, Eye swelling, Eye irritation, Eye pain, Ocular discomfort, Ocular hyperemia, Periorbital edema, Scleral hyperemia
- Gastrointestinal disorders: Dyspepsia
- Psychiatric disorders: Hallucinations
- Respiratory, thoracic and mediastinal disorders: Pneumonitis

Laboratory Abnormalities

All patients developed severe neutropenia, thrombocytopenia, and anemia. See Table 4 for the incidences of Grade 3 thrombocytopenia and Grade 4 neutropenia that were prolonged in the absence of active leukemia.

Table 4: Prolonged Cytopenias for Patients in Study 1
 | Induction 1 |  | Consolidation 1 b
 | VYXEOS; N=58; n (%) | 7+3; N=34; n (%) | VYXEOS; N=48; n (%) | 5+2; N=32; n (%)
Prolonged thrombocytopenia a | 16 (28) | 4 (12) | 12 (25) | 5 (16)
Prolonged neutropenia a | 10 (17) | 1 (3) | 5 (10) | 1 (3)

a Platelets < 50 Gi/L or neutrophils < 0.5 Gi/L lasting past cycle day 42 in the absence of active leukemia.

b Patients receiving at least 1 consolidation.

Grade 3-4 chemistry abnormalities occurring in greater than 5% of VYXEOS treated patients in Study 1 are presented in Table 5.

Table 5: Grade 3-4 a Chemistry Abnormalities ≥ 5% of VYXEOS Treated Patients in Study 1
 | Induction |  | Consolidation
 | VYXEOS; N=153; n (%) | 7+3; N=151; n (%) | VYXEOS; N=49; n (%) | 5+2; N=32; n (%)
Chemistry Abnormalities
Hyponatremia | 21 (14) | 20 (13) | 3 (6) | 0
Hypokalemia | 14 (9) | 19 (13) | 3 (6) | 2 (6)
Hypoalbuminemia | 11 (7) | 19 (13) | 1 (2) | 4 (13)
Hyperbilirubinemia | 9 (6) | 6 (4) | 1 (2) | 1 (3)
Alanine aminotransferase | 7 (5) | 8 (5) | 0 | 1 (3)

a Graded using NCI CTCAE version 3.0.

6.2 Postmarketing Experience

The following adverse reactions have been identified during postmarketing use of VYXEOS. Because these reactions are reported voluntarily from a population of uncertain size, it is not always possible to reliably estimate their frequency or establish a causal relationship to drug exposure: Infusion-related reactions

7 DRUG INTERACTIONS

7.1 Cardiotoxic Agents

Concomitant use of cardiotoxic agents may increase the risk of cardiotoxicity. Assess cardiac function more frequently when VYXEOS is coadministered with cardiotoxic agents [see Warnings and Precautions (5.3)].

7.2 Hepatotoxic Agents

Concomitant use with hepatotoxic agents may impair liver function and increase the toxicity of VYXEOS. Monitor hepatic function more frequently when VYXEOS is coadministered with hepatotoxic agents.

8 USE IN SPECIFIC POPULATIONS

8.1 Pregnancy

Risk Summary

Based on anecdotal data of cytarabine in pregnant women and results of studies of daunorubicin and cytarabine in animals, VYXEOS can cause embryo-fetal harm when administered to a pregnant woman. There are no adequate and well-controlled studies of VYXEOS, daunorubicin, or cytarabine in pregnant women. Daunorubicin and cytarabine are reproductive and developmental toxicants in multiple species (mice, rats, and/or dogs), starting at a dose that was approximately 0.02 times the exposure in patients at the recommended human dose on a mg/m^2 basis [see Animal Data]. Patients should be advised to avoid becoming pregnant while taking VYXEOS. If this drug is used during pregnancy, or if the patient becomes pregnant while taking this drug, apprise the patient of the potential harm to a fetus.

The estimated background risk of major birth defects and miscarriage for the indicated population is unknown. Adverse outcomes in pregnancy occur regardless of the health of the mother or the use of medications. In the U.S. general population, the estimated background risks of major birth defects and miscarriage in clinically recognized pregnancies are 2 to 4% and 15 to 20%, respectively.

Data

Human Data

Cytarabine can cause fetal harm if a pregnant woman is exposed to the drug. Four anecdotal cases of major limb malformations have been reported in infants after their mothers received intravenous cytarabine, alone or in combination with other agents, during the first trimester.

Animal Data

A liposomal formulation of daunorubicin was administered to rats on gestation days 6 through 15 at 0.3, 1.0, or 2.0 mg/kg/day (about 0.04, 0.14, or 0.27 the recommended human dose on a mg/m^2 basis) and produced severe maternal toxicity and embryolethality at 2.0 mg/kg/day and was embryotoxic and caused fetal malformations (anophthalmia, microphthalmia, incomplete ossification) at 0.3 mg/kg/day. Embryotoxicity was characterized by increased embryo-fetal deaths, reduced numbers of litters, and reduced litter sizes.

Cytarabine was teratogenic in mice (cleft palate, phocomelia, deformed appendages, skeletal abnormalities) when doses ≥ 2 mg/kg/day were administered intraperitoneal (IP) during the period of organogenesis (about 0.06 times the recommended human dose on a mg/m^2 basis), and in rats (deformed appendages) when 20 mg/kg was administered as a single IP dose on day 12 of gestation (about 1.2 times the recommended human dose on a mg/m^2 basis). Single IP doses of 50 mg/kg in rats (about 3 times the recommended human dose on a mg/m^2 basis) on day 14 of gestation reduced prenatal and postnatal brain size and permanent impairment of learning ability.

Cytarabine was embryotoxic in mice when administered during the period of organogenesis. Embryotoxicity was characterized by decreased fetal weight at 0.5 mg/kg/day (about 0.02 times the recommended human dose on a mg/m^2 basis), and increased early and late resorptions and decreased live litter sizes at 8 mg/kg/day (about 0.24 times the recommended human dose on a mg/m^2 basis).

8.2 Lactation

Risk Summary

There are no data on the presence of daunorubicin, cytarabine, or their metabolites in human milk, their effects on the breastfed infant, or their effects on milk production. Because of the potential for serious adverse reactions in breastfed infants, advise lactating women not to breastfeed during treatment with VYXEOS and for 2 weeks after the last dose.

8.3 Females and Males of Reproductive Potential

VYXEOS can cause fetal harm when administered to a pregnant woman [see Use in Specific Populations (8.1)].

Pregnancy Testing

Verify the pregnancy status of females of reproductive potential prior to initiating VYXEOS.

Contraception

Females

Advise females of reproductive potential to use effective contraception during treatment with VYXEOS and for 6 months after the last dose.

Males

Advise males with female partners of reproductive potential to use effective contraception during treatment with VYXEOS and for 6 months after the last dose [see Nonclinical Toxicology (13.1)].

Infertility

Based on findings of daunorubicin and cytarabine in animals, male fertility may be compromised by treatment with VYXEOS [see Nonclinical Toxicology (13.1)].

8.4 Pediatric Use

Newly Diagnosed t-AML or AML-MRC

The safety and effectiveness of VYXEOS have been established in pediatric patients 1 year and older with newly diagnosed t-AML or AML-MRC. The use of VYXEOS for this indication is supported by evidence of effectiveness from an adequate and well-controlled study in adults with data on safety from two single-arm trials, which included patients in the following age groups: 7 patients 1 year to less than 2 years old, 33 patients 2 years to less than 12 years old, 13 patients 12 years old to less than 17 years old. The exposures of total daunorubicin and cytarabine observed in pediatric patients were within the values observed in adults given the same dose based on body surface area [see Clinical Pharmacology (12.3)]. No new safety signals were observed in pediatric patients in these two single-arm trials. No differences in safety were observed by age. The safety and effectiveness of VYXEOS in pediatric patients less than 1 year of age with newly diagnosed t-AML or AML-MRC have not been established.

Newly Diagnosed de novo AML

The safety and effectiveness of VYXEOS in pediatric patients with de novo AML were assessed but not established in an open-label, randomized study (NCT04293562) comparing VYXEOS plus gemtuzumab ozogamicin to standard chemotherapy plus gemtuzumab ozogamicin. The VYXEOS arm included 324 pediatric patients less than 17 years old. No new safety signals were identified in the pediatric patients treated with VYXEOS and gemtuzumab ozogamicin in this trial.

8.5 Geriatric Use

Of the 375 patients who received VYXEOS (daunorubicin 44 mg/m^2 and cytarabine 100 mg/m^2) liposome in clinical studies, 57% were 65 years and over. No overall differences in safety were observed between these patients and younger patients, with the exception of bleeding events, which occurred more frequently in patients 65 years and older compared to younger patients (77% vs. 59%).

8.6 Renal Impairment

Dosage adjustment is not required for patients with mild (creatinine clearance [CLCR] 60 mL/min to 89 mL/min by Cockcroft Gault equation [C-G]), moderate (CLCR 30 mL/min to 59 mL/min) or severe (CLCR 15 mL/min to 29 mL/min) renal impairment. VYXEOS has not been studied in patients with end-stage renal disease on hemodialysis [see Clinical Pharmacology (12.3)].

8.7 Hepatic Impairment

Dosage adjustment is not required for patients with a bilirubin level less than or equal to 3 mg/dL. VYXEOS has not been studied in patients with bilirubin level greater than 3 mg/dL [see Clinical Pharmacology (12.3)].

11 DESCRIPTION

VYXEOS (daunorubicin and cytarabine) liposome for injection is a combination of daunorubicin and cytarabine in a 1:5 molar ratio encapsulated in liposomes for intravenous administration. The liposome membrane is composed of distearoylphosphatidylcholine (DSPC), distearoylphosphatidylglycerol (DSPG), and cholesterol in a 7:2:1 molar ratio.

Daunorubicin is an anthracycline topoisomerase inhibitor. The chemical name for daunorubicin is (1S,3S)-3-acetyl-1,2,3,4,6,11-hexahydro-3,5,12-trihydroxy-10-methoxy-6,11-dioxo-1-naphthacenyl-3-amino-2,3,6-trideoxy-α-L-lyxo-hexopyranoside; its molecular weight is 527.52. Daunorubicin has the following structural formula:

Cytarabine is a nucleoside metabolic inhibitor. The chemical name of cytarabine is 4-amino-1-β-D-arabinofuranosyl-2(1H)-pyrimidinone; its molecular weight is 243.22. Cytarabine has the following structural formula:

VYXEOS liposome for injection is supplied as a sterile, preservative-free, purple, lyophilized cake, in a single-dose vial. Each vial contains 44 mg daunorubicin and 100 mg cytarabine, and the following inactive ingredients: distearoylphosphatidylcholine 454 mg, distearoylphosphatidylglycerol 132 mg, cholesterol HP 32 mg, copper gluconate 100 mg, triethanolamine 4 mg, and sucrose 2054 mg.

12 CLINICAL PHARMACOLOGY

12.1 Mechanism of Action

VYXEOS (daunorubicin and cytarabine) liposome for injection is a liposomal formulation of daunorubicin and cytarabine at a fixed 1:5 molar ratio. The 1:5 molar ratio of daunorubicin:cytarabine has been shown to have synergistic effects at killing leukemia cells in vitro and in murine models. Daunorubicin has antimitotic and cytotoxic activity, which is achieved by forming complexes with DNA, inhibiting topoisomerase II activity, inhibiting DNA polymerase activity, affecting regulation of gene expression, and producing DNA-damaging free radicals. Cytarabine is a cell cycle phase-specific antineoplastic agent, affecting cells only during the S-phase of cell division. Cytarabine acts primarily through inhibition of DNA polymerase. Based on animal data, the liposomes enter and persist in the bone marrow, where they are taken up intact by bone marrow cells. In leukemia-bearing mice, the liposomes are taken up by leukemia cells to a greater extent than by normal bone marrow cells. After cellular internalization, liposomes undergo degradation releasing cytarabine and daunorubicin within the intracellular environment.

12.2 Pharmacodynamics

Cardiac Electrophysiology

At the therapeutic exposures with the recommended dosing regimen, no large mean changes in the QTc interval (i.e., > 20 msecs) were observed. An exposure-QTc analysis suggested no concentration-dependent QTc interval prolongation.

12.3 Pharmacokinetics

The pharmacokinetics of daunorubicin and cytarabine administered as VYXEOS were investigated in adult patients who received a dose of daunorubicin 44 mg/m^2 and cytarabine 100 mg/m^2 administered as a 90-minute intravenous infusion on days 1, 3, and 5. The pharmacokinetics of each drug was based on total plasma concentrations (i.e., encapsulated plus unencapsulated drug).

Following the dose administered on day 5, the mean (% coefficient of variation [CV]) maximum plasma concentration (Cmax) for daunorubicin was 26.0 (32.7%) mcg/mL and cytarabine was 62.2 (33.7%) mcg/mL. The mean (%CV) area under the curve (AUC) during one dosing interval for daunorubicin was 637 (38.4%) mcg∙h/mL and cytarabine was 1900 (44.3%) mcg∙h/mL.

The accumulation ratio was 1.3 for daunorubicin and 1.4 for cytarabine. There was no evidence of time-dependent kinetics or major departures from dose proportionality over the range of 1.3 mg/3 mg per m^2 to 59 mg/134 mg per m^2 (0.03 to 1.3 times the approved recommended dosage).

Distribution

The volume of distribution (%CV) for daunorubicin is 6.6 L (36.8%) and cytarabine is 7.1 L (49.2%). Plasma protein binding was not evaluated.

Elimination

VYXEOS exhibits a prolonged half-life (%CV) of 31.5 h (28.5%) for daunorubicin and 40.4 h (24.2%) for cytarabine with greater than 99% of the daunorubicin and cytarabine in the plasma remaining encapsulated within the liposomes. The clearance (%CV) is 0.16 L/h (53.3%) for daunorubicin and 0.13 L/h (60.2%) for cytarabine.

Metabolism

Subsequent to release from VYXEOS liposomes, daunorubicin is catalyzed by aldoketo reductase and carbonyl reductase enzymes to the active metabolite daunorubicinol. Cytarabine is metabolized by cytidine deaminase to the inactive metabolite 1-β-D-arabinofuranosyluracil (AraU).

Excretion

Urinary excretion of daunorubicin and daunorubicinol accounts for 9% of the administered dose of daunorubicin, and urinary excretion of cytarabine and AraU accounts for 71% of the administered dose of cytarabine.

Specific Populations

No clinically meaningful effects on the pharmacokinetics of daunorubicin and cytarabine were observed based on age (1 to 81 years), sex, race, body weight (9 to 156 kg), body mass index (14 to 48 kg/m^2), and white blood cell count (0.2 to 111 Gi/L) after adjusting dose by body surface area.

Pediatric Patients

The exposures of total daunorubicin and cytarabine observed in pediatric patients were within the values observed in adults given the same dose based on body surface area.

Geriatric Patients

The exposures of total daunorubicin and cytarabine observed in patients aged >65 years were within the values observed in patients aged 18 to 64 years given the same dose based on body surface area.

Patients with Renal Impairment

Comparing to patients with normal renal function (n=7, CLcr ≥ 90 mL/min), patients with moderate renal impairment (n=8, CLcr 30 to 59 mL/min) showed 8% and 6% decrease, respectively, in the mean AUCtau of total cytarabine and daunorubicin; patients with severe renal impairment (n=6, CLcr 15 to 29 mL/min) showed 0.4% increase and 3% decrease, respectively, in the mean AUCtau of cytarabine and daunorubicin in a dedicated study.

There are no data in patients with end-stage renal disease managed with hemodialysis.

Patients with Hepatic Impairment

The pharmacokinetics of total cytarabine and daunorubicin were not altered in patients with bilirubin less than and equal to 3 mg/dL. The pharmacokinetics in patients with bilirubin greater than 3 mg/dL is unknown.

13 NONCLINICAL TOXICOLOGY

13.1 Carcinogenesis, Mutagenesis, Impairment of Fertility

Carcinogenicity, mutagenicity, and impairment of fertility studies with VYXEOS (daunorubicin and cytarabine) liposome for injection have not been conducted.

Carcinogenicity and mutagenicity studies have been conducted with daunorubicin. Published literature reported data that suggest daunorubicin (5 mg/kg) could be tumorigenic in rats at 0.68 times the recommended human dose on a mg/m^2 basis. A high incidence of mammary tumors was observed about 120 days after a single intravenous dose of 12.5 mg/kg daunorubicin in rats (about 1.7 times the recommended human dose on a mg/m^2 basis). A carcinogenic evaluation of daunorubicin by the International Agency for Research on Cancer (IARC) Working Group classified daunorubicin as a possible human carcinogen based on sufficient evidence in animals and inadequate data in humans. Daunorubicin was mutagenic in in vitro tests (Ames assay, V79 hamster cell assay), and clastogenic in in vitro (CCRF-CEM human lymphoblasts) and in in vivo (sister-chromatid exchange (SCE) assay in mouse bone marrow) tests.

Daunorubicin intravenous doses of 0.25 mg/kg/day (about 0.12 times the recommended human dose on a mg/m^2 basis) in male dogs caused testicular atrophy and total aplasia of spermatocytes in the seminiferous tubules.

Cytarabine was mutagenic in in vitro tests and was clastogenic in vitro (chromosome aberrations and SCE in human leukocytes) and in vivo (chromosome aberrations and SCE assay in rodent bone marrow, mouse micronucleus assay). Cytarabine caused the transformation of hamster embryo cells and rat H43 cells in vitro.

No studies assessing the impact of cytarabine on fertility are available in the literature. Cytarabine was clastogenic to meiotic cells; a dose-dependent increase in sperm-head abnormalities and chromosomal aberrations occurred in mice given IP cytarabine.

14 CLINICAL STUDIES

Study 1

Study 1 (NCT01696084) was a randomized, multicenter, open-label, active-controlled study which compared VYXEOS to a standard combination of cytarabine and daunorubicin (7+3) in patients 60 to 75 years of age with newly diagnosed t-AML or AML-MRC. The patients were randomized (1:1) and stratified by age and AML sub-type to receive VYXEOS or 7+3 for induction and consolidation. VYXEOS (daunorubicin 44 mg/m^2 and cytarabine 100 mg/m^2) liposome was given intravenously on days 1, 3, and 5 for the first induction and on days 1 and 3 for the second induction if needed. For consolidation, the VYXEOS dose was (daunorubicin 29 mg/m^2 and cytarabine 65 mg/m^2) liposome on days 1 and 3. In the 7+3 arm, first induction consisted of cytarabine 100 mg/m^2/day on days 1 through 7 by continuous infusion and daunorubicin 60 mg/m^2/day on days 1, 2, and 3; for second induction and consolidation cycles, cytarabine 100 mg/m^2/day was given on days 1 through 5 and daunorubicin 60 mg/m^2/day on days 1 and 2. Patients could receive up to 2 cycles of induction and 2 cycles of consolidation in each arm. A second induction was highly recommended for patients who did not achieve a response and was mandatory for patients achieving greater than 50% reduction in percent blasts. Post remission therapy with hematopoietic stem cell transplantation (HSCT) was permitted either in place of or after consolidation chemotherapy.

There were 153 patients randomized to VYXEOS and 156 patients randomized to the 7+3 control arm. The randomized patients had a median age of 68 (range, 60-75 years), 61% were male, and 88% had an ECOG performance status of 0–1. Twenty percent had t-AML, 54% had AML with an antecedent hematological disorder, and 25% had de novo AML with myelodysplasia-related cytogenetic abnormalities. Thirty-four percent had been treated previously with a hypomethylating agent for myelodysplastic syndrome (MDS). Fifty-four percent of patients with cytogenetics data had an adverse karyotype. The demographic and baseline disease characteristics were generally balanced between the study arms. FLT3 mutation was identified in 15% (43/279) of patients tested, and NPM1 mutation was identified in 9% (25/283) patients tested.

All patients on the VYXEOS arm and 97% of those on the control arm received at least 1 cycle of induction, and 32% on the VYXEOS arm and 21% on the control arm received at least 1 cycle of consolidation. The rate of HSCT in first CR was 20% in the VYXEOS arm and 12% in the control arm; the overall rate of HSCT (induction failure, first CR, or as salvage after relapse) was 34% (52/153) in the VYXEOS arm and 25% (39/156) on the control arm.

Efficacy was established on the basis of overall survival from the date of randomization to death from any cause. VYXEOS demonstrated superiority in overall survival compared with the 7+3 control (Figure 1). The efficacy results are shown in Table 6.

Figure 1: Kaplan-Meier Curve for Overall Survival, ITT Population

Table 6: Efficacy Results for Study 1
 | VYXEOS; N=153 | 7+3; N=156
Overall Survival
Median survival, months (95% CI) | 9.6 (6.6, 11.9) | 5.9 (5.0, 7.8)
Hazard ratio (95% CI) | 0.69 (0.52, 0.90)
p–value (2–sided) a | 0.005
Complete Response Rate
CR, n (%) | 58 (38) | 41 (26)
p-value (2–sided) b | 0.036

Abbreviations: CI = Confidence interval; CR = Complete Remission

a p-value from stratified log rank test stratifying by age and AML sub-type

b p-value from Mantel-Haenszel test stratifying by age and AML sub-type

15 REFERENCES

1. OSHA Hazardous Drugs. OSHA. [Accessed on 15 June 2017, from http://www.osha.gov/SLTC/hazardousdrugs/index.html.]

16 HOW SUPPLIED/STORAGE AND HANDLING

How Supplied

VYXEOS (daunorubicin and cytarabine) liposome for injection is supplied as a sterile, preservative-free, purple, lyophilized cake, in a single-dose vial. Each VYXEOS vial (NDC 68727-745-01) contains 44 mg daunorubicin and 100 mg cytarabine.

NDC 68727-745-02: Carton containing 2 vials of VYXEOS

Storage

Store unreconstituted VYXEOS vials in a refrigerator at 2°C to 8°C (36°F to 46°F) in an upright position. The vial should be stored in its original carton to protect from light.

Handling and Disposal

VYXEOS is a hazardous drug. Follow applicable special handling and disposal procedures.^1

17 PATIENT COUNSELING INFORMATION

Hemorrhage

Inform patients of the risk of fatal bleeding. Advise patients of the need for periodic monitoring of blood counts and of the importance of keeping scheduled appointments for blood work and necessary transfusions. Advise patients to contact a healthcare provider for new onset fever or symptoms of infection or if they notice signs of bruising or bleeding [see Warnings and Precautions (5.2) and Adverse Reactions (6.1)].

Cardiotoxicity

Advise patients to contact their healthcare provider if they develop symptoms of heart failure [see Warnings and Precautions (5.3)].

Hypersensitivity Reactions

Inform patients of the risk of hypersensitivity reactions, including anaphylaxis. Describe the symptoms of hypersensitivity reactions, including anaphylaxis, and instruct the patient to seek medical attention immediately if they experience such symptoms [see Warnings and Precautions (5.4)].

Embryo-Fetal Toxicity

VYXEOS can cause fetal harm when administered during pregnancy. Advise females of reproductive potential to use effective contraception during treatment and for 6 months following the last dose of VYXEOS and to inform their healthcare provider of a known or suspected pregnancy before and during treatment with VYXEOS [see Warnings and Precautions (5.7) and Use in Specific Populations (8.1) and (8.3)].

Lactation

Advise patients not to breastfeed during treatment with VYXEOS and for 2 weeks after the last dose [see Use in Specific Populations (8.2)].

Infertility

Advise males of reproductive potential that VYXEOS may cause temporary or permanent infertility [see Use in Specific Populations (8.3)].

Concomitant Medications

Advise patients to speak with their physicians about any other medication they are currently taking [see Drug Interactions (7)].

This product's label may have been updated. For full prescribing information, please visit labels.fda.gov.

Distributed by:
Jazz Pharmaceuticals, Inc.
Palo Alto, CA 94306

Protected by U.S. Patent Nos. 7,238,367; 7,744,921; 7,850,990; 8,022,279; 8,092,828; 8,431,806; 8,518,437; 9,271,931; 10,028,912; 10,166,184; and 10,835,492

VYXEOS® is a trademark of Jazz Pharmaceuticals plc or its subsidiaries.

©2025 Jazz Pharmaceuticals www.vyxeos.com